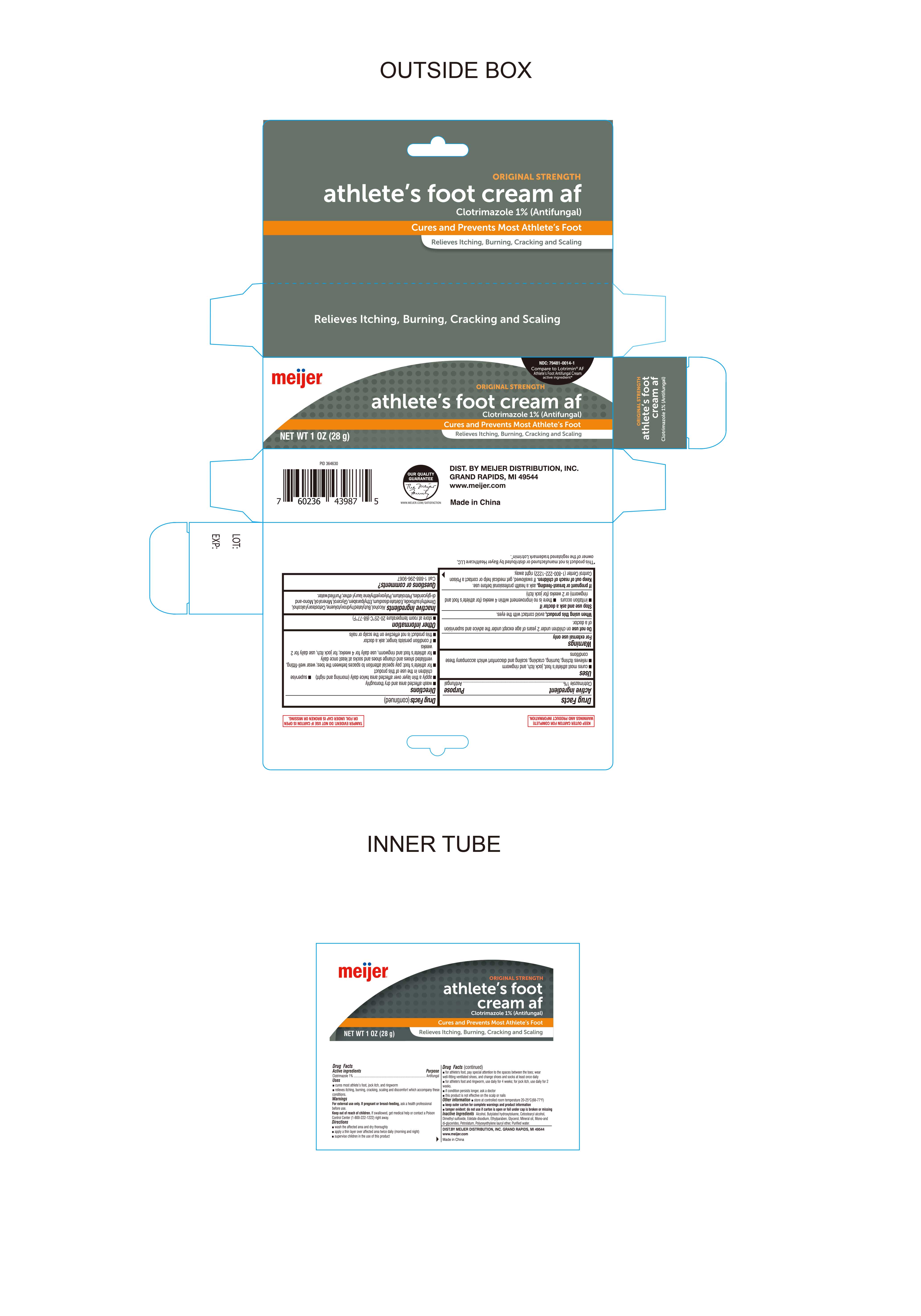 DRUG LABEL: Clotrimazole 1%
NDC: 79481-0014 | Form: CREAM
Manufacturer: Meijer
Category: otc | Type: HUMAN OTC DRUG LABEL
Date: 20230111

ACTIVE INGREDIENTS: CLOTRIMAZOLE 1 g/100 g
INACTIVE INGREDIENTS: CETOSTEARYL ALCOHOL; MINERAL OIL; ALCOHOL; BUTYLATED HYDROXYTOLUENE; DIMETHYL SULFOXIDE; ETHYLPARABEN; GLYCERIN; LAURETH-23; PETROLATUM; WATER; EDETATE DISODIUM; GLYCERYL MONO AND DIPALMITOSTEARATE

Meijer Athlete's Foot Cream af

Active ingredient

Clotrimazole 1%

Purpose

Antifungal

KEEP OUT OF REACH OF CHILDREN

Keep this and all drugs out of the reach of children. In case of accidental ingestion, seek professional assistance or contact a Poison Control right away.

Uses

Cures most athlete’s foot, jock itch and ringworm. Relieves itching, burning, cracking, scaling and discomfort which accompany these conditions.

Warnings

For External Use Only

● Do not use on children under 2 years of age except under the advice and supervision of a doctor.

● When using this product avoid contact with eyes.

Stop Use and ask a Doctor if:

- irritation occurs
- there is no improvement within 4 weeks (for Athlete's foot or ringwork) or 2 weeks (for jock itch).

Directions

- Wash the affected area and dry thoroughly.

● Apply a thin layer of this product over affected area twice daily.

● Supervise children in the use of this product.

● For athlete’s foot, pay special attention to the spaces between the toes; wear well-fitting ventilated shoes, and change shoes and socks at least once daily.

● For athlete’s foot and ringworm, use daily for 4 weeks. For jock itch, use daily for 2 weeks.

● If conditions persists longer, ask a doctor.

● This product is not effective on the scalp or nails.

Inactive Ingredients

Alcohol, Butylated Hydroxytoluene, Dimethyl Sulfoxide, Ethylparaben, Glycerol, Polyoxyethylene lauryl ether, Light Mineral Oil, Petrolatum, Cetostearyl Alcohol, purified Water, mono and di-glycerides, edetate disodium

Other Information

- store at room temperature 20°-25°C (68°- 77°F)

Questions or Comments?

DISTRIBUTED BY MEIJER DISTRIBUTION, INC.

GRAND RAPIDS, MI 49544

www. meijer.com

Made in China

This product is not manufactured or distributed by Bayer Healthcare LLC., owner of the registered trademark Lotrimin®.

If Pregnant or Breast-Feeding

Ask a Health Professional before use.

Keep out of reach of Children

If swallowed, get medical help or contact a Poison Control Center (1-800-222-1222) right away.